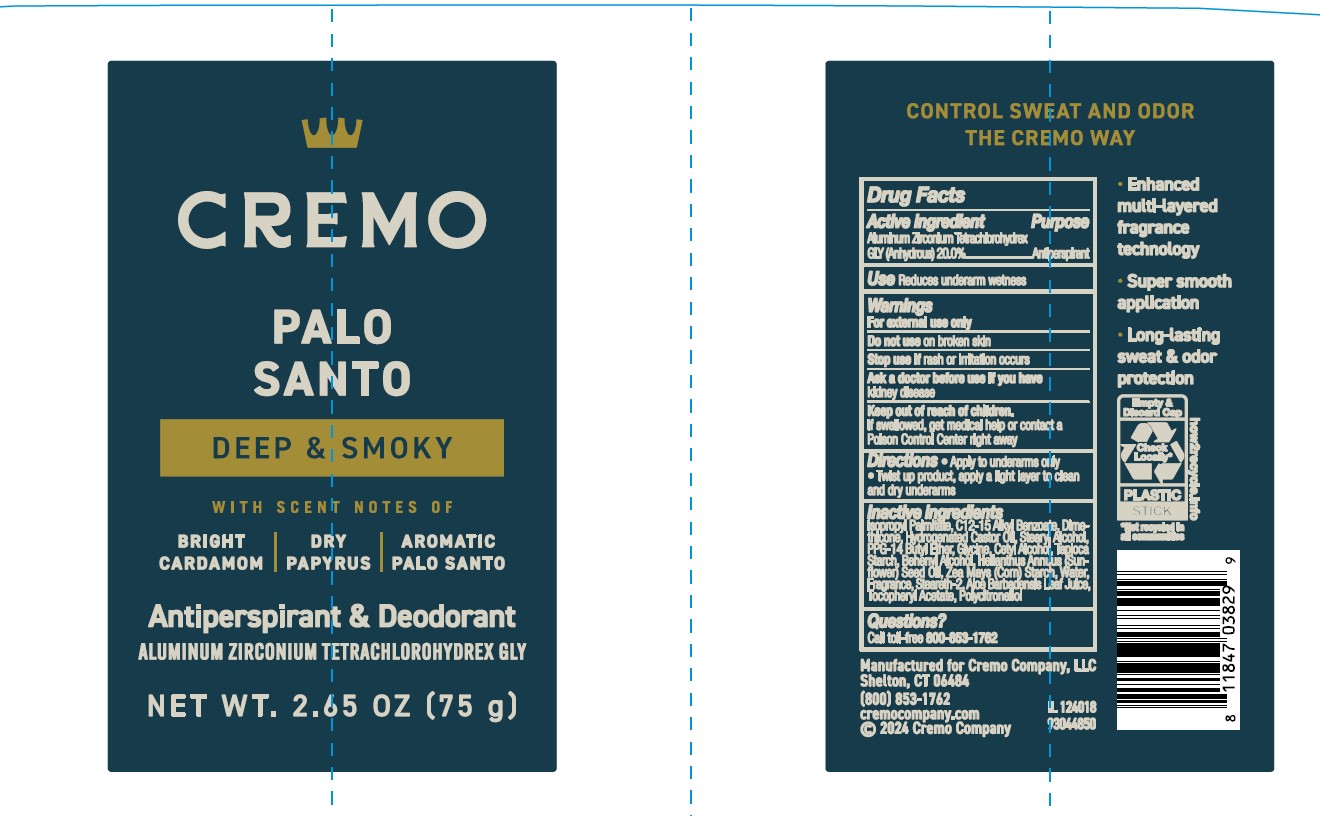 DRUG LABEL: Cremo Company
NDC: 71825-211 | Form: STICK
Manufacturer: Cremo Company
Category: otc | Type: HUMAN OTC DRUG LABEL
Date: 20241219

ACTIVE INGREDIENTS: ALUMINUM ZIRCONIUM TETRACHLOROHYDREX GLY 20 g/100 mL
INACTIVE INGREDIENTS: STEARYL ALCOHOL; PPG-14 BUTYL ETHER; HELIANTHUS ANNUUS (SUNFLOWER) SEED OIL; DIMETHICONE; WATER; BEHENYL ALCOHOL; STEARETH-2; HYDROGENATED CASTOR OIL; ISOPROPYL PALMITATE; C12-15 ALKYL BENZOATE; ALOE BARBADENSIS LEAF JUICE; GLYCINE; CETYL ALCOHOL; TAPIOCA STARCH; ZEA MAYS (CORN) STARCH; .ALPHA.-TOCOPHEROL ACETATE

Active ingredient

Aluminum Zirconium Tetrachlorohydrex GLY (Anhydrous) 20.0%

Purpose

Antiperspirant

Uses

Reduces underarm wetness

Warnings

For external use only

Do not use

on broken skin

Stop use if

rash or irritation occurs.

Ask a doctor before use if you have

kidney disease.

Keep out of reach of children.

If swallowed, get medical help or contact a Poison Control Center right away.

Directions

- Apply to underarms only
- Twist up product, apply a light layer to clean and dry underarms

Inactive ingredients

Isopropyl Palmitate, C12-15 Alkyl Benzoate, Dimethicone, Hydrogenated Castor Oil, Stearyl Alcohol, PPG-14 Butyl Ether, Glycine, Cetyl Alcohol, Tapioca Starch, Behenyl Alcohol, Helianthus Annuus (Sunflower) Seed Oil, Zea Mays (Corn) Starch, Water, Fragrance, Steareth-2, Aloe Barbadensis Leaf Juice, Tocopheryl Acetate, Polycitronellol.

Questions?

Call toll-free 800-853-1762

Primary Display Panel

Cremo
PALO SANTO
DEEP & SMOKEY
WITH SCENT NOTES OF
BRIGHT CARDAMOM | DRY PAPYRUS | AROMATIC PALO SANTO
Antiperspirant & Deodorant
ALUMINUM ZIRCONIUM TETRACHLOROHYDREX GLY
NET WT. 2.65 OZ (75 G)